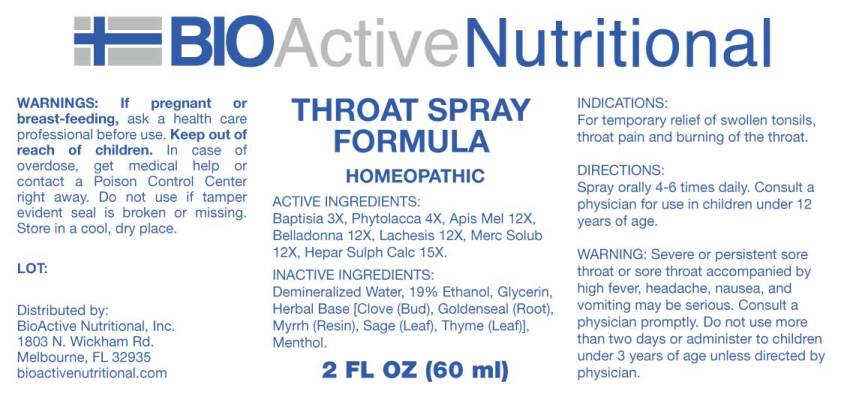 DRUG LABEL: Throat Formula
NDC: 43857-0484 | Form: SPRAY
Manufacturer: BioActive Nutritional, Inc.
Category: homeopathic | Type: HUMAN OTC DRUG LABEL
Date: 20250519

ACTIVE INGREDIENTS: BAPTISIA TINCTORIA 3 [hp_X]/1 mL; PHYTOLACCA AMERICANA ROOT 4 [hp_X]/1 mL; APIS MELLIFERA 12 [hp_X]/1 mL; ATROPA BELLADONNA 12 [hp_X]/1 mL; LACHESIS MUTA VENOM 12 [hp_X]/1 mL; MERCURIUS SOLUBILIS 12 [hp_X]/1 mL; CALCIUM SULFIDE 15 [hp_X]/1 mL
INACTIVE INGREDIENTS: CLOVE; SAGE; THYME; MYRRH; GOLDENSEAL; WATER; ALCOHOL; GLYCERIN; MENTHOL

Drug Facts:

ACTIVE INGREDIENTS:

Baptisia Tinctoria 3X, Phytolacca Decandra 4X, Apis Mellifica 12X, Belladonna 12X, Lachesis Mutus 12X, Mercurius Solubilis 12X, Hepar Sulphuris Calcareum 15X.

INDICATIONS:

For temporary relief of swollen tonsils, throat pain and burning of the throat.

WARNINGS:

If pregnant or breast-feeding, ask a health care professional before use.

Keep out of reach of children. In case of overdose, get medical help or contact a Poison Control Center right away.

Do not use if tamper evident seal is broken or missing.

Store in a cool, dry place.

Keep out of reach of children. In case of overdose, get medical help or contact a Poison Control Center right away.

DIRECTIONS:

Spray orally 4-6 times daily. Consult a physician for use in children under 12 years of age.

INDICATIONS:

For temporary relief of swollen tonsils, throat pain and burning of the throat.

INACTIVE INGREDIENTS:

Clove, Sage, Thyme, Myrrh, Goldenseal, Demineralized Water, 19% Ethanol, Glycerin, Menthol Crystals.

QUESTIONS:

Distributed by:
BioActive Nutritional, Inc.
1803 N. Wickham Rd.
Melbourne, FL 32935
bioactivenutritional.com

PACKAGE LABEL DISPLAY:

BIOActive Nutritional

THROAT SPRAY FORMULA

HOMEOPATHIC

2 FL OZ (60 ml)